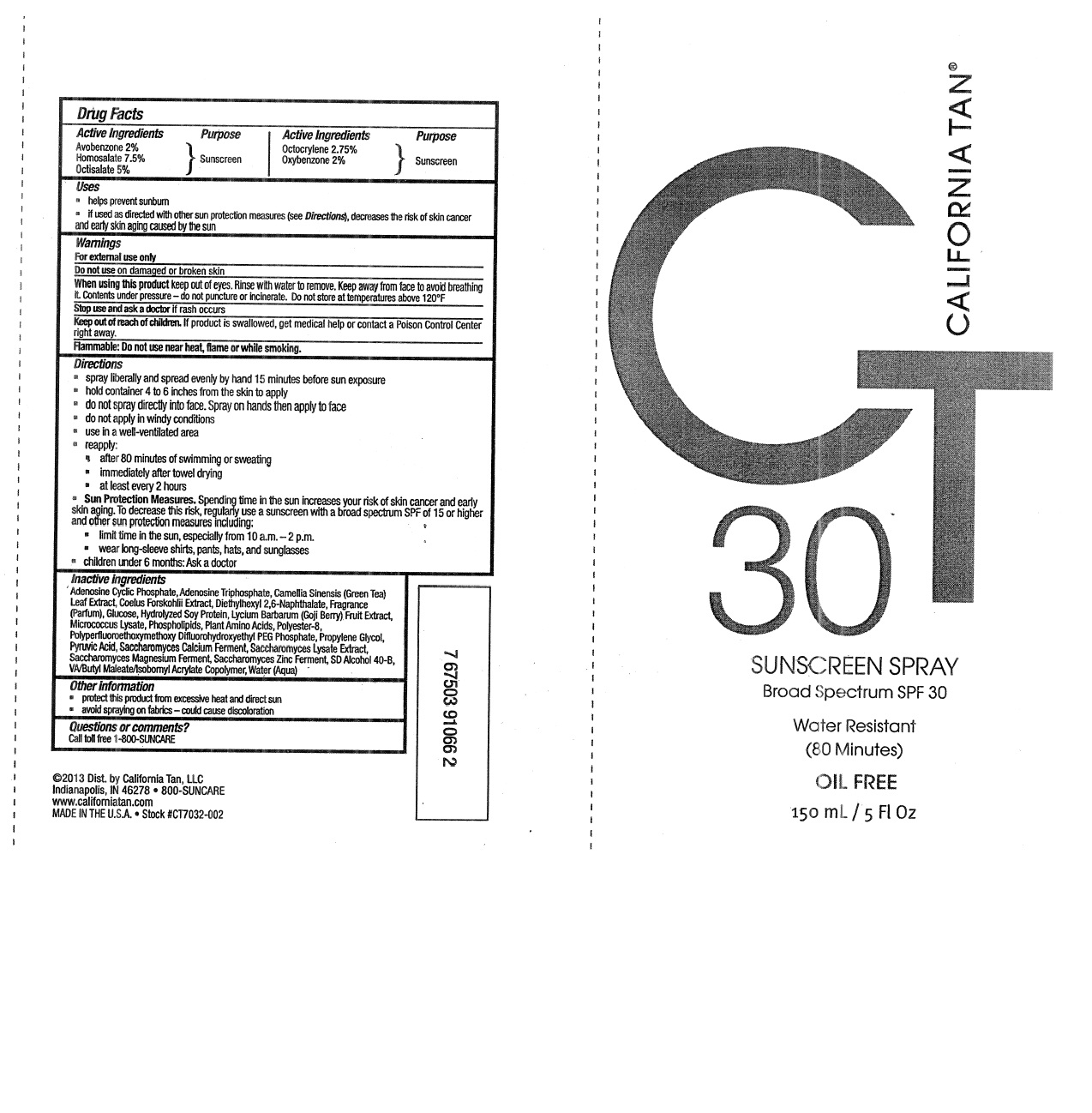 DRUG LABEL: California Tan
NDC: 13630-0112 | Form: SPRAY
Manufacturer: Prime Packaging Inc.
Category: otc | Type: HUMAN OTC DRUG LABEL
Date: 20200117

ACTIVE INGREDIENTS: AVOBENZONE 16.5 mg/1 mL; HOMOSALATE 62 mg/1 mL; OCTISALATE 41.3 mg/1 mL; OCTOCRYLENE 22.7 mg/1 mL; OXYBENZONE 16.5 mg/1 mL
INACTIVE INGREDIENTS: OMEGA-3 FATTY ACIDS; SACCHAROMYCES CEREVISIAE; ADENOSINE TRIPHOSPHATE; ALCOHOL; ADENOSINE CYCLIC PHOSPHATE; POLYESTER-8 (1400 MW, CYANODIPHENYLPROPENOYL CAPPED); PROPYLENE GLYCOL; HYDROLYZED SOY PROTEIN (ENZYMATIC; 2000 MW); PLECTRANTHUS BARBATUS ROOT; AMINO ACIDS; GREEN TEA LEAF; DIETHYLHEXYL 2,6-NAPHTHALATE; DEXTROSE; LYCIUM BARBARUM FRUIT; WATER; PYRUVIC ACID; SACCHAROMYCES LYSATE; DIBUTYL MALEATE; MICROCOCCUS LUTEUS

California Tan Continuous Sunscreen Broad Spectrum SPF 30

Active Ingredients

Avobenzone 2%

Homosalate 7.5%

Octisalate 5%

Octocrylene 2.75%

Oxybenzone 2%

Purpose

Sunscreen

Uses

- helps prevent sunburn
- if used as directed with other sun protection measures (see Directions), decreases the risk of skin cancer and early skin aging caused by the sun

Warnings

For external use only

Do not use on damaged or broken skin

When using this product keep out of eyes. Rinse with water to remove. Keep away from face to avoid breathing it

Contents under pressure - do not puncture or incinerate. Do not store at temperatures above 120°F

Stop use and ask a doctor if rash occurs

Keep out of reach of children. If product is swallowed, get medical help or contact a Poison Control Center right away.

Flammable: Do not use near heat, flame or while smoking.

Directions

- spray liberally and spread evenly by hand 15 minutes before sun exposure
- hold container 4 to 6 inches from the skin to apply
- do not spray directly into face. Spray on hands then apply to face
- do not apply in windy conditions
- use in a well-ventilated area
- reapply:
- after 80 minutes of swimming and sweating
- immediately after towel drying
- at least every 2 hours
- Sun Protection Measures. Spending time in the sun increases your risk of skin cancer and early skin aging. To decrease this risk, regularly use a sunscreen with a broad spectrum SPF of 15 or higher and other sun protection measures including:
- limit time in the sun, especially from 10 a. m. - 2 p. m.
- wear long-sleeve shirts, pants, hats, and sunglasses
- children under 6 months: Ask a doctor

INACTIVE INGREDIENT

Adenosine Cyclic Phosphate, Adenosine Triphosphate, Camellia Sinensis (Green Tea) Leaf Extract, Coleus Forskohlii Extract, Diethylhexyl 2,6-Naphthalate, Fragrance (Parfum), Glucose, Hydrolyzed Soy Protein, Lycium Barbarum (Goji Berry) Fruit Extract, Micrococcus Lysate, Phospholipids, Plant Amino Acids, Polyester-8, Polyperfluoroethoxymethoxy Difluorohydroxyethyl PEG Phosphate, Propylene Glycol, Pyruvic Acid, Saccharomyces Calcium Ferment, Saccharomyces Lysate Extract, Saccharomyces Magnesium Ferment, Saccharomyces Zinc Ferment, Alcohol Denat., VA/Butyl Maleate/Isobornyl Acrylate Copolymer, Water (Aqua)

Other Information

- protect this product from excessive heat and direct sun
- avoid spraying on fabrics - could cause discoloration

Question or comments?

Call toll free 1-800 SUNCARE